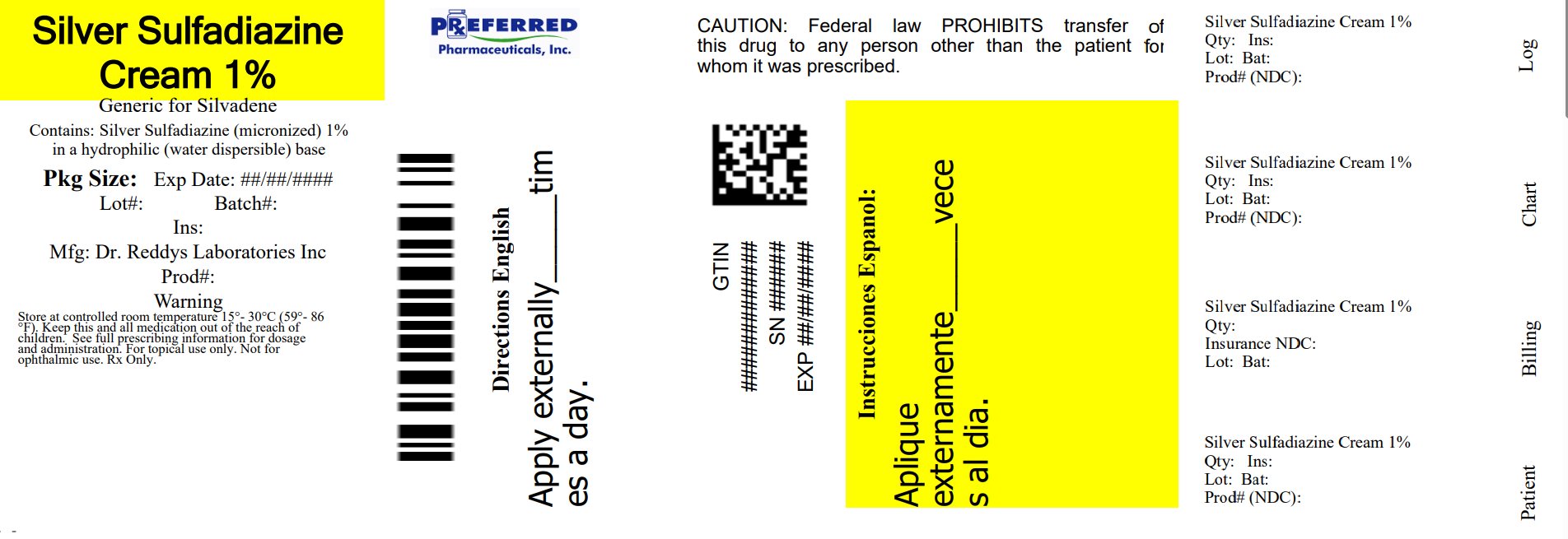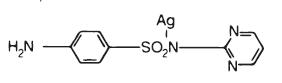 DRUG LABEL: SSD Cream
NDC: 68788-8074 | Form: CREAM
Manufacturer: Preferred Pharmaceuticals Inc.
Category: prescription | Type: HUMAN PRESCRIPTION DRUG LABEL
Date: 20250922

ACTIVE INGREDIENTS: Silver Sulfadiazine 10 g/1000 g
INACTIVE INGREDIENTS: WATER; CETYL ALCOHOL; STEARYL ALCOHOL; PETROLATUM; POLYOXYL 40 STEARATE TYPE I; PROPYLENE GLYCOL; ISOPROPYL MYRISTATE; SORBITAN MONOOLEATE; METHYLPARABEN

SSD™ (1% Silver Sulfadiazine Cream)
SSD AF™ (1% Silver Sulfadiazine Cream)

DESCRPITION

SSD™ (1% Silver Sulfadiazine Cream) and SSD AF™ (1% Silver Sulfadiazine Cream), 1% are topical antibacterial preparations which have as their active antimicrobial ingredient silver sulfadiazine. The active moiety is contained within an opaque, white, water miscible cream base.
Each 1000 grams of SSD/SSD AF Cream contains 10 grams of silver sulfadiazine.
Inactive Ingrediants: cetyl alcohol (SSD Cream only), isopropyl myristate, polyoxyl 40 stearate, propylene glycol, purified water, stearyl alcohol, sodium hydroxide, sorbitan monooleate, white petrolatum; with 0.3% methyl paraben, as a preservative.
Silver sulfadiazine has an emprical formula of C10H9AgN4O2S, molecular weight of 357.14 and structural formula as shown:

CLINICAL PHARMACOLOGY

Silver sulfadiazine has broad antimicrobial activity. It is bactericidal for many gram-negative and gram-positive bacteria as well as being effective against yeast. Results from in vitro testing are listed below. Sufficient data have been obtained to demonstrate that silver sulfadiazine will inhibit bacteria that are resistant to other antimicrobial agents and that the compound is superior to sulfadiazine. Studies utilizing radioactive micronized silver sulfadiazine, electron microscopy, and biochemical techniques have revealed that the mechanism of action of silver sulfadiazine on bacteria differs from silver nitrate and sodium sulfadiazine. Silver sulfadiazine acts only on the cell wall to produce its bactericidal effect.

Results of In Vitro Testing With Silver Sulfadiazine Cream, 1% Concentration of Silver Sulfadiazine
Number of Sensitive Strains / Total Number of Strains Tested

Genus and Species 50 micrograms/mL 100 micrograms/mL

Xanthomonas (Pseudomonas)

Maltophilia 7/7 7/7

Enterobacter Species 48/50 50/50

Enterobacter cloacae 24/24 24/24

Klebsiella Species 53/54 54/54

Escherichia Coli 63/63 63/63

Serratia Species 27/28 28/28

Proteus Mirabilis 53/53 53/53

Morganella Morganii 10/10 10/10

Providencia Rettgeri 2/2 2/2

Proteus Vulgaris 2/2 2/2

Providencia Species 1/1 1/1

Citrobacter Species 10/10 10/10

Acinetobacter Calcoaceticus 10/11 11/11

Clostridium Perfringens 0/2 2/2

Clostridium Perfringens 0/2 2/2

Candida Albicans 43/50 50/50

Silver sulfadiazine is not a carbonic anhydrase inhibitor and may be useful in situations where such agents are contraindicated.

INDICATIONS AND USAGE

Silver Sulfadiazine Cream is a topical antimicrobial drug indicated as an adjunct for the prevention and treatment of wound sepsis in patients with second and third degree burns.

CONTRAINDICATIONS

Silver Sulfadiazine Cream is contraindicated in patients who are hypersensitive to silver sulfadiazine or any of the other ingredients in the preparation.

Because sulfonamide therapy is known to increase the possibility of kernicterus, Silver Sulfadiazine Cream should not be used on pregnant women approaching or at term, on premature infants, or on newborn infants during the first 2 months of life.

WARNING

There is a potential cross-sensitivity between silver sulfadiazine and other sulfonamides. If allergic reactions attributable to treatment with silver sulfadiazine occur, continuation of therapy must be weighed against the potential hazards of the particular allergic reaction.

Fungal proliferation in and below the eschar may occur. However, the incidence of clinically reported fungal superinfection is low.

The use of Silver Sulfadiazine Cream in some cases of glucose-6-phosphate dehydrogenase-deficient individuals may be hazardous, as hemolysis may occur.

PRECAUTION

If hepatic and renal functions become impaired and elimination of the drug decreases accumulation may occur and discontinuation of Silver Sulfadiazine Cream should be weighed against the therapeutic benefit being achieved.

In considering the use of topical proteolytic enzymes in conjunction with Silver Sulfadiazine Cream, the possibility should be noted that silver may inactivate such enzymes.

Laboratory Tests: In the treatment of burn wounds involving extensive areas of the body, the serum sulfa concentrations may approach adult therapeutic levels (8 to 12mg %). Therefore, in these patients it would be advisable to monitor serum sulfa concentrations. Renal function should be carefully monitored and the urine should be checked for sulfa crystals.

Absorption of the propylene glycol vehicle has been reported to affect serum osmolality, which may affect the interpretation of laboratory tests.

Carcinogenesis, Mutagenesis, Impairment of Fertility

Long-term dermal toxicity studies of 24 months duration in rats and 18 months in mice with concentrations of silver sulfadiazine three to ten times the concentration in Silver Sulfadiazine Cream revealed no evidence of carcinogenicity.

Pregnancy: Pregnancy Category B. A reproductive study has been performed in rabbits at doses up to three to ten times the concentration of silver sulfadiazine in Silver Sulfadiazine Cream and has revealed no evidence of harm to the fetus due to silver sulfadiazine. There are, however, no adequate and well-controlled studies in pregnant women. Because animal reproduction studies are not always predictive of human response, this drug should be used during pregnancy only if clearly justified, especially in pregnant women approaching or at term. (See CONTRAINDICATIONS)

Nursing Mother: It is not known whether Silver Sulfadiazine Cream is excreted in human milk. However, sulfonamides are known to be excreted in human milk and all sulfonamides derivatives are known to increase the possibility of kernicterus. Because of the potential for serious adverse reactions in nursing infants from sulfonamides, a decision should be made whether to discontinue nursing or to discontinue the drug, taking into account the importance of the drug to the mother.

Pediatric Use: Safety and effectiveness in children have not been established. (See CONTRAINDICATIONS)

ADVERSE REACTIONS

Several cases of transient leucopenia have been reported in patients receiving silver sulfadiazine therapy. Leucopenia associated with silver sulfadiazine administration is primarily characterized by decreased neutrophil count. Maximal white blood cell depression occurs within two to four days of initiation of therapy. Rebound to normal leukocyte levels follows onset within two to three days. Recovery is not influenced by continuation of silver sulfadiazine therapy. The incidence of leucopenia in various reports averages about 20%. A higher incidence has been seen in patients treated concurrently with cimetidine.

Other infrequently occurring events include skin necrosis, erythema multiforme, skin discoloration, burning sensation, rashes, and interstitial nephritis. Reduction in bacterial growth after application of topical antibacterial agents has been reported to permit spontaneous healing of deep partial thickness burns by preventing conversion of the partial thickness to full thickness by sepsis. However, reduction in bacterial colonization has caused delayed separation, in some cases necessitating escharotomy in order to prevent contracture.

Absorption of silver sulfadiazine varies depending upon the percent of body surface area and the extent of the tissue damage. Although few have been reported, it is possible that any adverse reaction associated with sulfonamides may occur. Some of the reactions which have been associated with sulfonamides are as follows: blood dyscrasias, agranulocytosis, aplastic anemia, thrombocytopenia, leucopenia, hemolytic anemia, dermatologic reactions, allergic reactions, Stevens-Johnson syndrome, exfoliative dermatitis, gastrointestinal reactions, hepatitis, hepatocellular necrosis, CNS reactions, and toxic nephrosis.

DOSAGE AND ADMINISTRATION: FOR TOPICAL USE ONLY - NOT FOR OPHTHALMIC USE:

Prompt institution of appropriate regimens for care of the burned patient is of prime importance and includes the control of shock and pain. The burn wounds are then cleansed and debrided; Silver Sulfadiazine Cream is then applied under sterile conditions. The burn areas should be covered with Silver Sulfadiazine Cream at all times. The cream should be applied once to twice daily to a thickness of approximately one sixteenth of an inch. Whenever necessary, the cream should be reapplied to any areas from which it has been removed due to patient activity. Administration may be accomplished in minimal time because dressings are not required. However, if individual patient requirements make dressings necessary, they may be used. Reapply immediately after hydrotherapy. Treatment with Silver Sulfadiazine Cream should be continued until satisfactory healing has occurred or until the burn site is ready for grafting. The drug should not be withdrawn from the therapeutic regimen while there remains the possibility of infection except if a significant adverse reaction occurs.

HOW SUPPLIED

SSD™ (1% Silver Sulfadiazine) Cream: white to off-white cream.

50 gram jar NDC 68788-8074- 5

25 gram tube NDC 68788-8074-2

Store at controlled room temperature 15° - 30°C (59° - 86°F)

SSD is a trademark of Dr. Reddy's Laboratories, Inc.
Manufactured by:
Dr. Reddy's Laboratories Louisiana LLC
Shreveport, LA 71106 USA

Revised, June 2013

Relabeled By: Preferred Pharmaceuticals Inc.

Container Label for 25 g Tube

SSD™
NDC 43598-210-25
Dr. Reddy’s
25 Grams
1% Silver Sulfadiazine Cream 1%
FOR TOPICAL USE ONLY
NOT FOR OPHTHALMIC USE
Rx Only
Silver Sulfadiazine…10mg/g
in a hydrophilic base consisting of cetyl alcohol, isopropyl myristate, polyoxyl 40 stearate, propylene glycol, purified water, stearyl alcohol, sodium hydroxide, sorbitan monooleate, white petrolatum; with 0.3% methylparaben, as a preservative. See full prescribing information for dosage and administration.
Store at controlled room 15° - 30°C (59° - 86°F).
SSD is a trademark of Dr. Reddy’s Laboratories, Inc.
Manufactured by
Dr. Reddy's Laboratories Louisiana, LLC
Shreveport, LA 71106 USA

Relabeled By: Preferred Pharmaceuticals Inc.